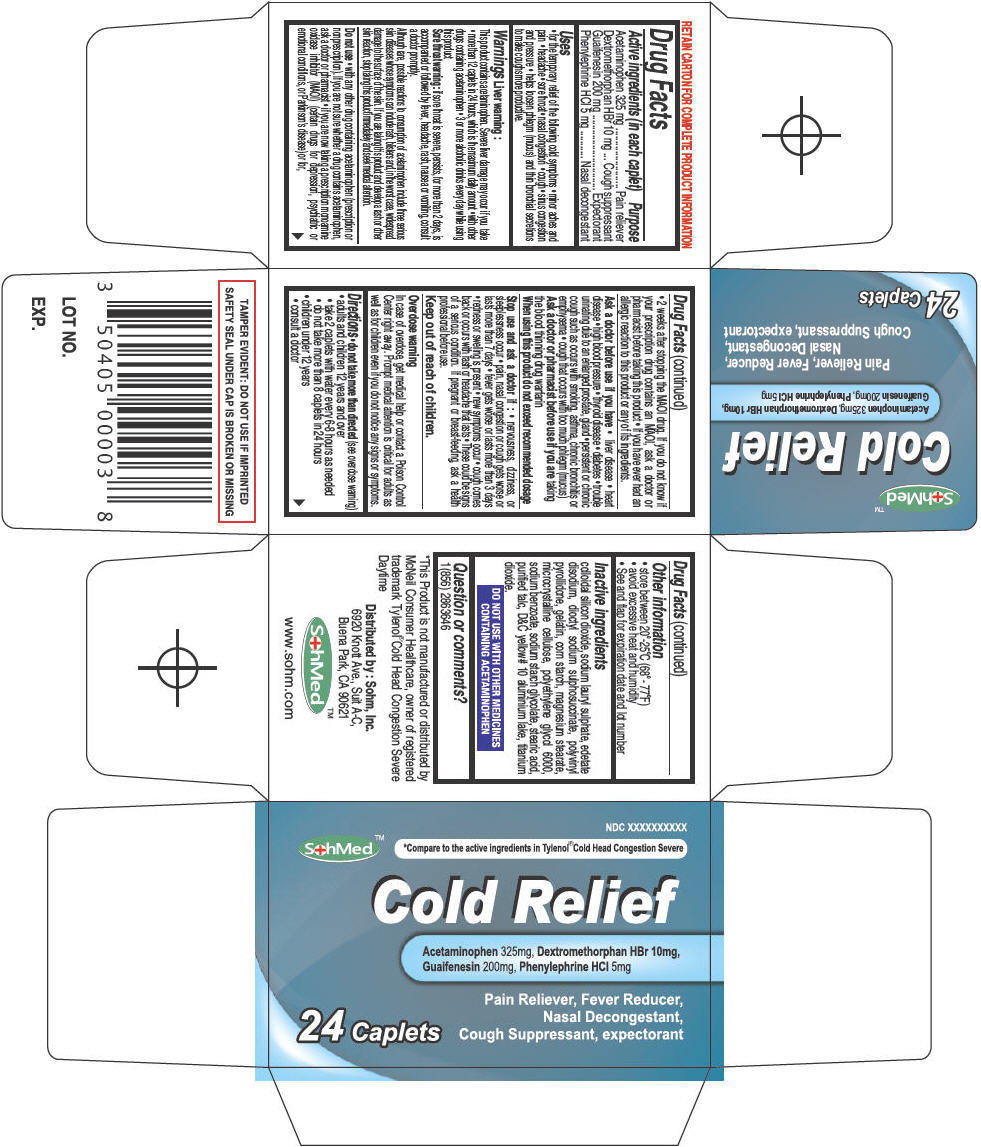 DRUG LABEL: SohMed Cold Relief
NDC: 50405-006 | Form: TABLET
Manufacturer: SOHM Inc.
Category: otc | Type: HUMAN OTC DRUG LABEL
Date: 20130820

ACTIVE INGREDIENTS: Acetaminophen 325 mg/1 1; Dextromethorphan Hydrobromide 10 mg/1 1; Guaifenesin 200 mg/1 1; Phenylephrine Hydrochloride 5 mg/1 1
INACTIVE INGREDIENTS: SILICON DIOXIDE; SODIUM LAURYL SULFATE; EDETATE DISODIUM; DOCUSATE SODIUM; STARCH, CORN; POVIDONE K90; GELATIN; MAGNESIUM STEARATE; CELLULOSE, MICROCRYSTALLINE; POLYETHYLENE GLYCOL 6000; SODIUM BENZOATE; SODIUM STARCH GLYCOLATE TYPE A CORN; STEARIC ACID; TALC; D&C YELLOW NO. 10; ALUMINUM OXIDE; TITANIUM DIOXIDE

SohMed™ Cold Relief

Drug Facts

ACTIVE INGREDIENT

Active ingredients (in each caplet) | Purpose
Acetaminophen 325 mg | Pain reliever
Dextromethorphan HBr 10 mg | Cough suppressant
Guaifenesin 200 mg | Expectorant
Phenylephrine HCl 5 mg | Nasal decongestant

Uses

- for the temporary relief of the following cold symptoms
- minor aches and pain
- headache
- sore throat
- nasal congestion
- cough
- sinus congestion and pressure
- helps loosen phlegm (mucus) and thin bronchial secretions to make coughs more productive.

Warnings

Liver warning

This product contains acetaminophen. Severe liver damage may occur if you take

- more than 12 caplets in 24 hours, which is the maximum daily amount
- with other drugs containing acetaminophen
- 3 or more alcoholic drinks every day while using this product

Sore throat warning : if sore throat is severe, persists, for more than 2 days, is accompanied or followed by fever, headache, rash, nausea or vomiting, consult a doctor promptly.

Although rare, possible reactions to consumption of acetaminophen include three serious skin diseases whose symptoms can include rash, blisters and, in the worst case, widespread damage to the surface of the skin. If you are taking this product and develop a rash or other skin reaction, stop taking this product immediately and seek medical attention.

Do not use

- with any other drug containing acetaminophen (prescription or nonprescription). If you are not sure whether a drug contains acetaminophen, ask a doctor or pharmacist
- if you are now taking a prescription monoamine oxidase inhibitor (MAOI) (certain drugs for depression, psychiatric or emotional conditions, or Parkinson's disease) or for,
  - 2 weeks after stopping the MAOI drug. If you do not know if your prescription drug contains an MAOI, ask a doctor or pharmacist before taking this product
  - If you have ever had an allergic reaction to this product or any of its ingredients.

Ask a doctor before use if you have

- liver disease
- heart disease
- high blood pressure
- thyroid disease
- diabetes
- trouble urinating due to an enlarged prostate, gland
- persistent or chronic cough such as occurs with smoking, asthma, chronic bronchitis or emphysema
- cough that occurs with too much phlegm (mucus)

Ask a doctor or pharmacist before use if you are taking the blood thinning drug warfarin

When using this product do not exceed recommended dosage

Stop use and ask a doctor if

- nervousness, dizziness, or sleeplessness occur
- pain, nasal congestion or cough gets worse or lasts more than 7 days
- fever gets worse or lasts more than 3 days
- redness or swelling is present
- new symptoms occur
- cough comes back or occurs with rash or headache that lasts
- These could be signs of a serious condition.

PREGNANCY OR BREAST FEEDING

If pregnant or breast-feeding, ask a health professional before use.

Keep out of reach of children.

Overdose warning

In case of overdose, get medical help or contact a Poison Control Center right away. Prompt medical attention is critical for adults as well as for children even if you do not notice any signs or symptoms.

Directions

- do not take more than directed (see overdose warning)
- adults and children 12 years and over
  - take 2 caplets with water every 6-8 hours as needed
  - do not take more than 8 caplets in 24 hours
- children under 12 years
  - consult a doctor

Other information

- store between 20°-25°C (68°- 77°F)
- avoid excessive heat and humidity
- See and flap for expiration date and lot number

Inactive ingredients

colloidal silicon dioxide, sodium lauryl sulphate, edetate disodium, dioctyl sodium sulphosuccinate, polyvinyl pyrollidone, gelatin, corn starch, magnesium stearate, microcrystalline cellulose, polyethylene glycol 6000, sodium benzoate, sodium starch glycolate, stearic acid, purified talc, D&C yellow# 10 aluminium lake, titanium dioxide.

DO NOT USE WITH OTHER MEDICINES CONTAINING ACETAMINOPHEN

Question or comments?

1(856) 2863646

Distributed by : Sohm, Inc.
6920 Knott Ave., Suit A-C,
Buena Park, CA 90621

PRINCIPAL DISPLAY PANEL - 24 Tablet Bottle Carton

NDC XXXXXXXXXX

SohMed™
*Compare to the active ingredients in Tylenol® Cold Head Congestion Severe

Cold Relief

Acetaminophen 325mg, Dextromethorphan HBr 10mg,
Guaifenesin 200mg, Phenylephrine HCl 5mg

24 Caplets

Pain Reliever, Fever Reducer,
Nasal Decongestant,
Cough Suppressant, expectorant